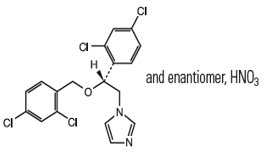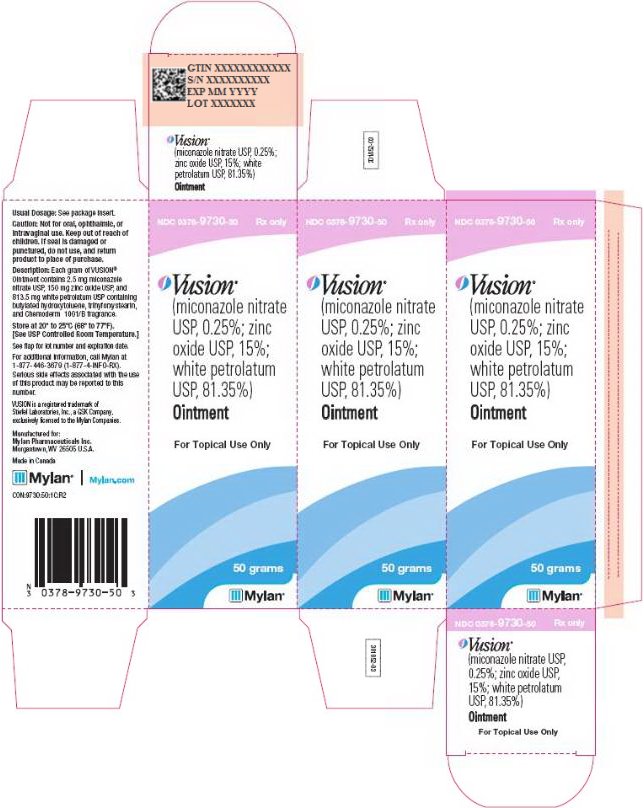 DRUG LABEL: VUSION
NDC: 0378-9730 | Form: OINTMENT
Manufacturer: Mylan Pharmaceuticals Inc.
Category: prescription | Type: HUMAN PRESCRIPTION DRUG LABEL
Date: 20180815

ACTIVE INGREDIENTS: MICONAZOLE NITRATE 2.5 mg/1 g; ZINC OXIDE 150 mg/1 g; PETROLATUM 813.5 mg/1 g
INACTIVE INGREDIENTS: BUTYLATED HYDROXYTOLUENE; TRIHYDROXYSTEARIN

HIGHLIGHTS OF PRESCRIBING INFORMATION

These highlights do not include all the information needed to use VUSION Ointment safely and effectively. See full prescribing information for VUSION Ointment.
VUSION® (miconazole nitrate, zinc oxide, and white petrolatum) ointment, for topical use
Initial U.S. Approval: 2006

1 INDICATIONS AND USAGE

- VUSION Ointment is indicated for adjunctive treatment of diaper dermatitis when complicated by documented candidiasis (microscopic evidence of pseudohyphae and /or budding yeast) in immunocompetent pediatric patients 4 weeks and older. (1.1)
- VUSION Ointment should not be used as a substitute for frequent diaper changes. (1.1)
- VUSION Ointment should not be used to prevent the occurrence of diaper dermatitis, since preventative use may result in the development of drug resistance. (1.2)

2 DOSAGE AND ADMINISTRATION

- VUSION Ointment is for topical use only. VUSION Ointment is not for oral, ophthalmic, or intravaginal use. (2)
- VUSION Ointment should be applied as a thin layer to the affected area at each diaper change for 7 days. (2)
- VUSION Ointment should be used as part of a treatment regimen that includes gentle cleansing of the diaper area and frequent diaper changes. (2)

3 DOSAGE FORMS AND STRENGTHS

- Ointment with 0.25% miconazole nitrate, 15% zinc oxide, and 81.35% white petrolatum. (3)

4 CONTRAINDICATIONS

- None

5 WARNINGS AND PRECAUTIONS

- If irritation occurs or if the disease worsens, discontinue use of the medication, and contact the health care provider. (5.1)

6 ADVERSE REACTIONS

To report SUSPECTED ADVERSE REACTIONS, contact Mylan at 1-877-446-3679 (1-877-4-INFO-RX) or FDA at 1-800-FDA-1088 or www.fda.gov/medwatch.

FULL PRESCRIBING INFORMATION

1 INDICATIONS AND USAGE

1.1 Indication

VUSION Ointment is indicated for the adjunctive treatment of diaper dermatitis only when complicated by documented candidiasis (microscopic evidence of pseudohyphae and/or budding yeast), in immunocompetent pediatric patients 4 weeks and older. A positive fungal culture for Candida albicans is not adequate evidence of candidal infection since colonization with C. albicans can result in a positive culture. The presence of candidal infection should be established by microscopic evaluation prior to initiating treatment.

VUSION should be used as part of a treatment regimen that includes measures directed at the underlying diaper dermatitis, including gentle cleansing of the diaper area and frequent diaper changes. VUSION should not be used as a substitute for frequent diaper changes.

1.2 Limitations of Use

The safety and efficacy of VUSION have not been demonstrated in immunocompromised patients, or in infants less than 4 weeks of age (premature or term).

The safety and efficacy of VUSION have not been evaluated in incontinent adult patients. VUSION should not be used to prevent the occurrence of diaper dermatitis, such as in an adult institutional setting, since preventative use may result in the development of drug resistance.

2 DOSAGE AND ADMINISTRATION

VUSION is not for oral, ophthalmic, or intravaginal use.

Before applying VUSION, gently cleanse the skin with lukewarm water and pat dry with a soft towel. Avoid using any scented soaps, shampoos, or lotions on the diaper area.

Gently apply a thin layer of VUSION to the diaper area with each diaper change for 7 days. Do not rub VUSION into the skin as this may cause additional irritation. Thoroughly wash hands after applying VUSION. Continue treatment for the full 7 days, even if there is improvement.

Do not use VUSION for longer than 7 days. The safety of VUSION when used for longer than 7 days is not known. If symptoms have not improved by day 7, see your health care provider.

3 DOSAGE FORMS AND STRENGTHS

VUSION (miconazole nitrate, zinc oxide and white petrolatum) contains 2.5 mg of miconazole nitrate USP, 150 mg of zinc oxide USP and 813.5 mg of white petrolatum USP per gram.

4 CONTRAINDICATIONS

None

5 WARNINGS AND PRECAUTIONS

5.1 Skin Irritation

If irritation occurs or if the disease worsens, discontinue use of the medication, and contact the health care provider.

6 ADVERSE REACTIONS

6.1 Clinical Trials Experience

Because clinical trials are conducted under widely varying conditions, adverse reaction rate observed in the clinical trials of a drug cannot be directly compared to rates in the clinical trials of another drug and may not reflect the rates observed in clinical practice.

A total of 835 infants and young children were evaluated in the clinical development program. Of 418 subjects in the VUSION group, 58 (14%) reported one or more adverse events. Of 417 subjects in the zinc oxide/white petrolatum control group, 85 (20%) reported one or more adverse events. Adverse events that occurred at a rate of ≥ 1% for subjects who were treated with VUSION were approximately the same in type and frequency as for subjects who were treated with zinc oxide/white petrolatum ointment.

6.2 Post-marketing Experience

The following adverse reactions have been identified during post approval use of VUSION. Because these reactions are reported voluntarily from a population of uncertain size, it is not always possible to reliably estimate their frequency or establish a causal relationship to drug exposure.

Gastrointestinal Disorders: vomiting

General Disorders and Administration Site Conditions: burning sensation, condition aggravated, inflammation, pain

Injury, Poisoning and Procedural Complications: accidental exposure

Skin and Subcutaneous Tissue Disorders: blister, dermatitis contact, diaper dermatitis, dry skin, erythema, pruritus, rash, skin exfoliation

7 DRUG INTERACTIONS

Drug-drug interaction studies were not conducted. Women who take a warfarin anticoagulant and use a miconazole intravaginal cream or suppository may be at risk for developing an increased prothrombin time, international normalized ratio (INR), and bleeding. The potential for this interaction between warfarin and VUSION is unknown.

8 USE IN SPECIFIC POPULATIONS

8.1 Pregnancy

Risk Summary

There are no available data on VUSION Ointment use in pregnant women to inform a drug‑associated risk for adverse developmental outcomes. In animal reproduction studies, prolonged gestation, increased number of resorptions, and decreased numbers of live young were observed after oral administration of miconazole nitrate during organogenesis to pregnant rats and rabbits. No comparisons of animal exposure with human exposure may be calculated due to minimal systemic exposure in humans after topical administration of VUSION [see Clinical Pharmacology (12.3)].

In the U.S. general population, the estimated background risk of major birth defects and miscarriage in clinically recognized pregnancies is 2 to 4% and 15 to 20%, respectively.

Data

Animal Data

Miconazole nitrate administration has been shown to result in prolonged gestation and decreased numbers of live young in rats and in increased number of resorptions and decreased number of live young in rabbits at oral doses of 100 mg/kg/day and 80 mg/kg/day.

8.2 Lactation

Risk Summary

There is no available information on the presence of miconazole in human milk, or the effects on the breastfed child, or the effects on milk production following use of VUSION.

The developmental and health benefits of breastfeeding should be considered along with the mother’s clinical need for VUSION and any potential adverse effects on the breastfed infant from VUSION or from the underlying maternal condition.

8.4 Pediatric Use

Efficacy was not demonstrated in infants less than 4 weeks of age. Safety and efficacy have not been established in very-low-birth-weight infants (less than 1500 g).

VUSION should not be used to prevent diaper dermatitis.

The safety of VUSION when used for longer than 7 days is not known. Do not use more than 7 days.

8.5 Geriatric Use

Safety and efficacy in a geriatric population have not been evaluated.

11 DESCRIPTION

VUSION contains the synthetic antifungal agent, miconazole nitrate (0.25%) USP, zinc oxide (15%) USP, and white petrolatum (81.35%) USP.

The chemical name of miconazole nitrate is 1-[2, 4-dichloro-ß-{(2,4-dichlorobenzyl)oxy} phenethyl] imidazole mononitrate with empirical formula C18H14Cl4N2O•HNO3 and molecular weight of 479.15. The structural formula of miconazole nitrate is as follows:

The zinc oxide has an empirical formula of ZnO and a molecular weight of 81.39.

The white petrolatum, which is obtained from petroleum and is wholly or nearly decolorized, is a purified mixture of semisolid saturated hydrocarbons having the general chemical formula CnH2n+2. The hydrocarbons consist mainly of branched and unbranched chains. White petrolatum contains butylated hydroxytoluene (BHT) as stabilizer.

Each gram of VUSION contains 2.5 mg of miconazole nitrate USP, 150 mg of zinc oxide USP, and 813.5 mg of white petrolatum USP containing butylated hydroxytoluene, trihydroxystearin, and Chemoderm 1001/B fragrance.

VUSION is a smooth, uniform, white ointment.

12 CLINICAL PHARMACOLOGY

12.1 Mechanism of Action

The miconazole component of VUSION is an antifungal agent [see Clinical Pharmacology (12.4)]. The mechanism of action of white petrolatum and zinc oxide for the adjunctive treatment of diaper dermatitis is unknown.

12.2 Pharmacodynamics

The human pharmacodynamics of Vusion is unknown [see Clinical Pharmacology (12.4) for fungal pharmacodynamics].

12.3 Pharmacokinetics

The topical absorption of miconazole from VUSION was studied in immunocompetent male and female infants and children (n=17) with diaper dermatitis complicated by documented candidiasis (microscopic evidence of pseudohyphae and/or budding yeast) ranging in age from 1 month to 21 months. After multiple daily applications to the affected area at every diaper change (approximately 5-12 times per day) for 7 days, the plasma concentrations of miconazole were below the lower limit of quantitation (LOQ) of 0.5 ng/mL in 15 out of 17 (88%) subjects. In the other 2 remaining subjects, the plasma concentrations of miconazole were 0.57 and 0.58 ng/mL, respectively at a single timepoint (4 hours after the last application) on Day 7.

12.4 Microbiology

The miconazole nitrate component in this product has been shown to have in vitro activity against Candida albicans, an organism that is associated with diaper dermatitis. The activity of miconazole nitrate against C. albicans is based on the inhibition of the ergosterol biosynthesis in the cell membrane. The accumulation of ergosterol precursors and toxic peroxides results in cytolysis of the cell. In vitro minimal inhibitory concentration (MIC) test results for C. albicans isolates obtained from treatment failures in Clinical Study 1 [see Clinical Studies (14)] does not appear to indicate that resistance to miconazole nitrate was the reason for treatment failure. The clinical significance of the in vitro activity of miconazole nitrate against C. albicans in the setting of diaper dermatitis is unclear.

13 NONCLINICAL TOXICOLOGY

13.1 Carcinogenesis, Mutagenesis, Impairment of Fertility

The carcinogenic potential of VUSION in animals has not been evaluated.

Miconazole nitrate was negative in a bacterial reverse mutation test, a chromosome aberration test in mice, and micronucleus assays in mice and rats.

Miconazole nitrate had no adverse effect on fertility in a study in rats at oral doses of up to 320 mg/kg/day.

14 CLINICAL STUDIES

Study 1 was a double-blind, multicenter study in which VUSION was compared to the zinc oxide and white petrolatum combination treatment and included 236 infants and toddlers with diaper dermatitis, complicated by candidiasis as documented by KOH tests that demonstrated pseudohyphae and/or budding yeasts. Study medication was applied at every diaper change for 7 days.

The primary endpoint was “Overall Cure” and required that subjects be both clinically cured (total resolution of all signs and symptoms of infection) and microbiologically cured (eradication of candidiasis). Primary efficacy was assessed 1 week following the end of treatment, at Day 14.

Study results are shown in the following table.

Overall Cure at Day 14
 | VUSION n=112 | Zinc Oxide/White Petrolatum n=124
 | 26 (23%) | 12 (10%)

Two additional studies provided supportive evidence of the clinical efficacy of VUSION in infants and toddlers with diaper dermatitis, some of whom cultured positive for C. albicans. However, candidal infection was not documented in the culture-positive subjects, as microscopic testing (e.g. KOH) was not done. Therefore, the positive culture results may have reflected colonization rather than infection.

16 HOW SUPPLIED/STORAGE AND HANDLING

16.1 How Supplied

VUSION (miconazole nitrate, zinc oxide and white petrolatum) contains 2.5 mg of miconazole nitrate USP, 150 mg of zinc oxide USP and 813.5 mg of white petrolatum USP per gram. The smooth, uniform, white ointment supplied in an aluminum tube is available as follows:

NDC 0378-9730-50
carton containing one 50 gram tube

16.2 Storage Conditions

Store at 20° to 25°C (68° to 77°F). [See USP Controlled Room Temperature.]

Keep out of reach of children.

17 PATIENT COUNSELING INFORMATION

See FDA-Approved Patient Labeling

Patients using VUSION should be informed about the following information:

- VUSION should be used only as directed by the health care provider.
- VUSION should not be used as a substitute for frequent diaper changes.
- VUSION should not be used to prevent diaper dermatitis.
- VUSION is for external use only. It is not for oral, ophthalmic, or intravaginal use.
- Gently cleanse the diaper area with lukewarm water or a very mild soap and pat the area dry with a soft towel before applying VUSION.
- Gently apply VUSION to the diaper area with the fingertips after each diaper change. Do not rub VUSION into the skin as this may cause additional irritation.
- Thoroughly wash hands after applying VUSION.
- Treatment should be continued for 7 days, even if there is improvement. Do not use VUSION for longer than 7 days. If symptoms have not improved by day 7, see your health care provider.
- VUSION should not be used on children for whom it is not prescribed.

Patient Information

VUSION® (Vu-sion)
(miconazole nitrate, zinc oxide, and white petrolatum) Ointment

Important Information: VUSION is for use on the skin only. Do not use VUSION in the eyes, mouth, or vagina.

What is VUSION?
VUSION Ointment is a prescription medicine used on the skin (topical) to treat children 4 weeks of age and older with a normal immune system who have diaper rash (dermatitis) and who also have a yeast infection (candidiasis).

- Your child’s healthcare provider should do a test to check to make sure that your child also has a yeast infection before starting treatment with VUSION.
- VUSION should be used along with gentle cleaning of the diaper area and changing your child’s diaper often. See, “How should I use VUSION?” for detailed instructions on how to use VUSION the right way.
- VUSION should not be used to prevent diaper rash from developing (preventative treatment). Using VUSION as preventative treatment may cause VUSION to no longer work (resistance).

It is not known if VUSION is safe and effective for use in incontinent adults.

It is not known if VUSION is safe and effective for use in children less than 4 weeks of age or very low birth weight (less than 1500 grams).

Before using VUSION, tell your child’s healthcare provider about all their medical conditions..

How should I use VUSION?

- Use VUSION exactly as your child’s healthcare provider tells you to use it.
- Gently clean the skin on your child’s diaper area with warm (not hot) water and pat the area dry with a soft towel.
- Using your fingertips, apply a thin layer of VUSION to the affected area at each diaper change for 7 days. Do not rub VUSION into your child’s skin. Rubbing the skin can cause more irritation.
- Wash your hands after applying VUSION.
- VUSION should be used for the full 7 days of treatment. Do not stop treatment before the full 7 days, even if the symptoms improve.
- VUSION should not be used for longer than 7 days. Call your child’s healthcare provider if the diaper rash gets worse or does not go away with 7 days of treatment with VUSION.
- Call your child’s healthcare provider or poison control center right away if VUSION is swallowed or gets in the eyes.

What should I avoid while using VUSION?

- Avoid using scented soaps, shampoos or lotions in the diaper area during treatment with VUSION.

What are the possible side effects of VUSION?

VUSION may cause serious side effects, including:

- Skin irritation. Stop using VUSION and call your child’s healthcare provider if your child’s diaper rash gets worse or if your child develops skin irritation at the application site during treatment with VUSION.

These are not all the possible side effects of VUSION. Call your doctor for medical advice about side effects. You may report side effects to FDA at 1-800-FDA-1088.

How should I store VUSION?

- Store VUSION at room temperature between 68° to 77°F (20° to 25°C).
- Keep VUSION and all medicines out of the reach of children.

General information about the safe and effective use of VUSION.
Medicines are sometimes prescribed for purposes other than those listed in a Patient Information leaflet. Do not use VUSION for a condition for which it was not prescribed. Do not give VUSION to other people, even if they have the same symptoms your child has. It may harm them. You can ask your child’s healthcare provider or pharmacist for information about VUSION that is written for healthcare professionals.

What are the ingredients in VUSION?
Active Ingredients: miconazole nitrate, zinc oxide, and white petrolatum
Inactive Ingredients: trihydroxystearin, butylated hydroxytoluene (BHT), and Chemoderm 1001/B fragrance

Manufactured for: Mylan Pharmaceuticals Inc., Morgantown, WV 26505 U.S.A.

This Patient Information leaflet has been approved by the U.S. Food and Drug Administration. Revised: 8/2018

VUSION is a registered trademark of Stiefel Laboratories, Inc., a GSK Company, exclusively licensed to the Mylan Companies.

©2018 Mylan Pharmaceuticals Inc. All rights reserved.

Manufactured for:
Mylan Pharmaceuticals Inc.
Morgantown, WV 26505 U.S.A.

Manufactured by:
Confab Laboratories, Inc.
Saint-Hubert, QC, Canada

Revised: 8/2018
CON:MZPOIN:R1

PRINCIPAL DISPLAY PANEL – 50 grams

NDC 0378-9730-50 Rx only

Vusion®
(miconazole nitrate
USP, 0.25%; zinc
oxide USP, 15%;
white petrolatum
USP, 81.35%)
Ointment

For Topical Use Only

50 grams

Usual Dosage: See package insert.

Caution: Not for oral, ophthalmic, or
intravaginal use. Keep out of reach of
children. If seal is damaged or
punctured, do not use, and return
product to place of purchase.

Description: Each gram of VUSION®
Ointment contains 2.5 mg miconazole
nitrate USP, 150 mg zinc oxide USP, and
813.5 mg white petrolatum USP containing
butylated hydroxytoluene, trihyforxystearin,
and Chemoderm 1001/B fragrance.

Store at 20º to 25ºC (68º to 77ºF).
[See USP Controlled Room Temperature.]

See flap for lot number and expiration date.

For additional information, call Mylan at
1-877-446-3679 (1-877-4-INFO-RX).

Serious side effects associated with the use
of this product may be reported to this
number.

VUSION is a registered trademark of
Stiefel Laboratories, Inc., a GSK Company,
exclusively licensed to the Mylan Companies.

Manufactured for:
Mylan Pharmaceuticals Inc.
Morgantown, WV 26505 U.S.A.

Made in Canada

Mylan.com

CON:9730:50:1C:R2